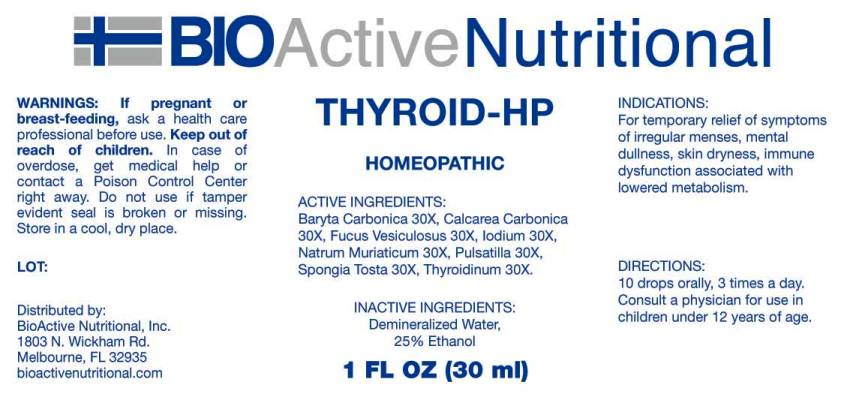 DRUG LABEL: Thyroid HP
NDC: 43857-0037 | Form: LIQUID
Manufacturer: BioActive Nutritional, Inc.
Category: homeopathic | Type: HUMAN OTC DRUG LABEL
Date: 20161101

ACTIVE INGREDIENTS: BARIUM CARBONATE 30 [hp_X]/1 mL; OYSTER SHELL CALCIUM CARBONATE, CRUDE 30 [hp_X]/1 mL; FUCUS VESICULOSUS 30 [hp_X]/1 mL; IODINE 30 [hp_X]/1 mL; SODIUM CHLORIDE 30 [hp_X]/1 mL; PULSATILLA VULGARIS 30 [hp_X]/1 mL; SPONGIA OFFICINALIS SKELETON, ROASTED 30 [hp_X]/1 mL; SUS SCROFA THYROID 30 [hp_X]/1 mL
INACTIVE INGREDIENTS: WATER; ALCOHOL

Drug Facts:

ACTIVE INGREDIENTS:

Baryta Carbonica 30X, Calcarea Carbonica 30X, Fucus Vesiculosus 30X, Iodium 30x, Natrum Muriaticum 30X, Pulsatilla 30X, Spongia Tosta 30X, Thyroidinum (Suis) 30X.

INDICATIONS:

For temporary relief of symptoms of irregular menses, mental dullness, skin dryness, immune dysfunction associated with lowered metabolism.

WARNINGS:

If pregnant or breast-feeding, ask a health care professional before use.

Keep out of reach of children. In case of overdose, get medical help or contact a Poison Control Center right away.

Do not use if tamper evident seal is broken or missing.

Store in cool, dry place.

DIRECTIONS:

10 drops orally, 3 times a day. Consult a physician for use in children under 12 years of age.

INACTIVE INGREDIENTS:

Demineralized Water, 25% Ethanol.

Keep out of reach of children. In case of overdose, get medical help or contact a Poison Control Center right away.

INDICATIONS:

For temporary relief of symptoms of irregular menses, mental dullness, skin dryness, immune dysfunction associated with lowered metabolism.

QUESTIONS:

Distributed by:
BioActive Nutritional, Inc.
1803 N. Wickham Rd.
Melbourne, FL 32935
bioactivenutritional.com

PACKAGE LABEL DISPLAY:

BIOActive Nutritional

THYROID HP

HOMEOPATHIC

1 FL OZ (30 ml)